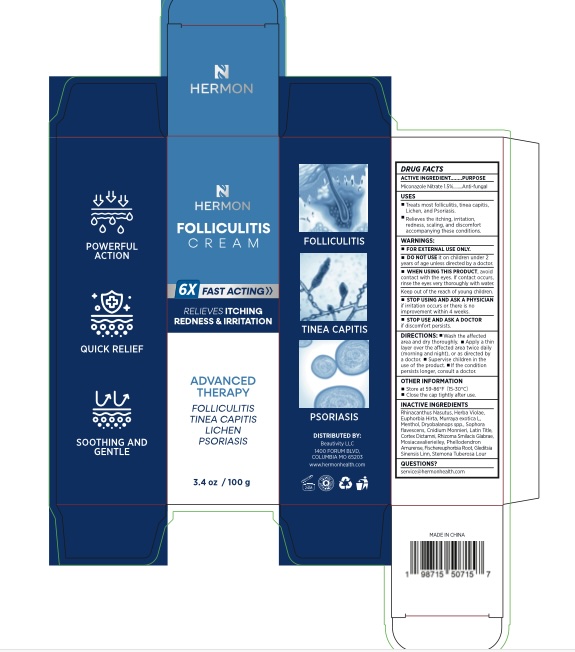 DRUG LABEL: Folliculitis Cream
NDC: 85398-001 | Form: CREAM
Manufacturer: Beautivity LLC
Category: otc | Type: HUMAN OTC DRUG LABEL
Date: 20250628

ACTIVE INGREDIENTS: MICONAZOLE NITRATE 1.5 g/100 g
INACTIVE INGREDIENTS: VIOLA PHILIPPICA WHOLE; PEPPERMINT; CNIDIUM MONNIERI FRUIT; GLYCERYL MONOSTEARATE; MURRAYA PANICULATA WHOLE; DIMETHICONE; BASSIA SCOPARIA WHOLE; DIANTHUS SUPERBUS FLOWERING TOP; MINERAL OIL; SOPHORA FLAVESCENS ROOT; GLYCERIN; STEARIC ACID; DICTAMNUS DASYCARPUS ROOT BARK; PETROLATUM; WATER; RHINACANTHUS NASUTUS LEAF; SMILAX GLABRA TUBER; PEG-100 STEARATE; EUPHORBIA HIRTA; BORNEOL; CHLORHEXIDINE ACETATE

Initial Drug Listing - Hermon Folliculitis Cream

ACTIVE INGREDIENT

Miconazole Nitrate 1.5%

PURPOSE

Anti-fungal

INDICATIONS AND USAGE

- Treats most folliculitis, tinea capitis, lichen, and psoriasis.
- Relieves the itching, irritation, redness, scaling and discomfort accompanying thee conditions.

WARNINGS

For external use only

DO NOT USE

it on children under 2 years of age unless directed by a doctor.

WHEN USING

avoid contact with eyes. If contact occurs, rinse the eyes thoroughly with water.
keep out of the reach of Children.

STOP USE

If irritation occurs or there is no improvement within 4 weeks.

DOSAGE AND ADMINISTRATION

- Wash the affected area and dry thoroughly.
- Apply a thin layer over the affected area twice daily (morning and night), or as directed by a doctor.
- Supervise children in the use of the product.
- If the condition persists longer, consult a doctor.

OTHER SAFETY INFORMATION

- Store at 59-85 ºF(15-30 ºC)
- Close the cap tightly after use

INACTIVE INGREDIENT

Water, Dimethicone, Mineral Oil, Petrolatum, Glycerin, Glyceryl Monostearate, Glyceryl Stearate, PEG-100 Stearate, Stearic Acid, Rhinacanthus nasutus Leaf, Viola philippica Whole, Euphorbia hirta Whole, Murraya paniculata Whole, Mentha haplocalyx Oil, Borneol, Sophora flavescens Root, Cnidium monnieri Fruit, Bassia scoparia Whole, Dictamnus dasycarpus Root Bark, Smilax glabra Tuber, Dianthus superbus Flowering Top, Chlorhexidine Acetate

QUESTIONS

contact us at service@hermonhealth.com

KEEP OUT OF REACH OF CHILDREN

If swallowed, get medical help or contact a Poison Control Center right away.